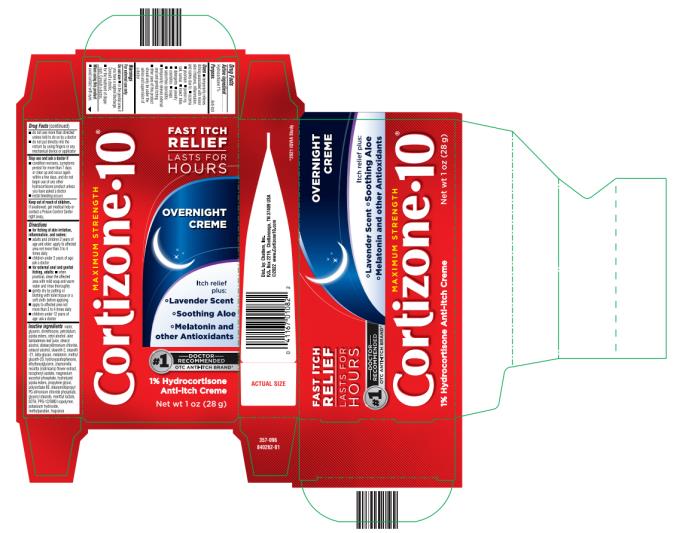 DRUG LABEL: Cortisone 10 Overnight Creme
NDC: 41167-0109 | Form: CREAM
Manufacturer: Chattem, Inc.
Category: otc | Type: HUMAN OTC DRUG LABEL
Date: 20231106

ACTIVE INGREDIENTS: HYDROCORTISONE 1 g/100 g
INACTIVE INGREDIENTS: WATER; GLYCERIN; DIMETHICONE; PETROLATUM; CETYL ALCOHOL; ALOE VERA LEAF; STEARYL ALCOHOL; DISTEARYLDIMONIUM CHLORIDE; CETOSTEARYL ALCOHOL; STEARETH-2; STEARETH-21; MELATONIN; METHYL GLUCETH-20; HYDROXYACETOPHENONE; ETHYLHEXYLGLYCERIN; CHAMOMILE; .ALPHA.-TOCOPHEROL ACETATE; MAGNESIUM ASCORBYL PHOSPHATE; PROPYLENE GLYCOL; POLYSORBATE 60; STEARAMIDOPROPYL PG-DIMONIUM CHLORIDE PHOSPHATE; GLYCERYL MONOSTEARATE; MENTHYL LACTATE, (-)-; EDETIC ACID; PPG-12/SMDI COPOLYMER; POTASSIUM HYDROXIDE; METHYLPARABEN; HYDROLYZED JOJOBA ESTERS (ACID FORM); TRANSFORMING GROWTH FACTOR BETA RECEPTOR TYPE 3

Cortizone 10 Overnight Creme

Cortizone 10 Overnight Relief

Drug Facts

Purpose

Hydrocortisone 1%...........................................................................................................................................Anti-itch

Uses

■ temporarily relieves itching associated with minor skin irritations, inflammation, and rashes due to:

■ eczema ■ psoriasis ■ poison ivy, oak, sumac ■ insect bites ■ detergents ■ jewelry ■ cosmetics

■ soaps ■ seborrheic dermatitis

■ temporarily relieves external anal and genital itching

■ other uses of this product should only be under the advice and supervision of a doctor

Warnings

For external use only

Do not use

■ in the genital area if you have a vaginal discharge. Consult a doctor.

■ for the treatment of diaper rash. Consult a doctor.

When using this product

■ avoid contact with eyes

■ do not use more than directed unless told to do so by a doctor

■ do not put directly into the rectum by using fingers or any mechanical device or applicator

Stop use and ask a doctor if

■ condition worsens, symptoms persist for more than 7 days or clear up and occur again within a few days, and do not begin use of any other hydrocortisone product unless you have asked a doctor

■ rectal bleeding occurs

Keep out of reach of children.

If swallowed, get medical help or contact a Poison Control Center right away.

Directions

■ for itching of skin irritation, inflammation, and rashes:

■ adults and children 2 years of age and older: apply to affected area not more than 3 to 4 times daily

■ children under 2 years of age: ask a doctor

■ for external anal and genital itching, adults:

■ when practical, clean the affected area with mild soap and warm water and rinse thoroughly

■ gently dry by patting or blotting with toilet tissue or a soft cloth before applying

■ apply to affected area not more than 3 to 4 times daily

■ children under 12 years of age: ask a doctor

Inactive ingredients

water, glycerin, dimethicone, petrolatum, jojoba esters, cetyl alcohol, aloe barbadensis leaf juice, stearyl alcohol, distearyldimonium chloride, cetearyl alcohol, steareth-2, steareth-21, beta-glucan, melatonin, methyl gluceth-20, hydroxyacetophenone, ethylhexylglycerin, chamomilla recutita (matricaria) flower extract, tocopheryl acetate, magnesium ascorbyl phosphate, hydrolyzed jojoba esters, propylene glycol, polysorbate 60, stearamidopropyl PG-dimonium chloride phosphate, glyceryl stearate, menthyl lactate, EDTA, PPG-12/SMDI copolymer, potassium hydroxide, methylparaben, fragrance

PRINCIPAL DISPLAY PANEL

Cortizone 10
Overnight Crème
Net wt 1 oz (28 g)